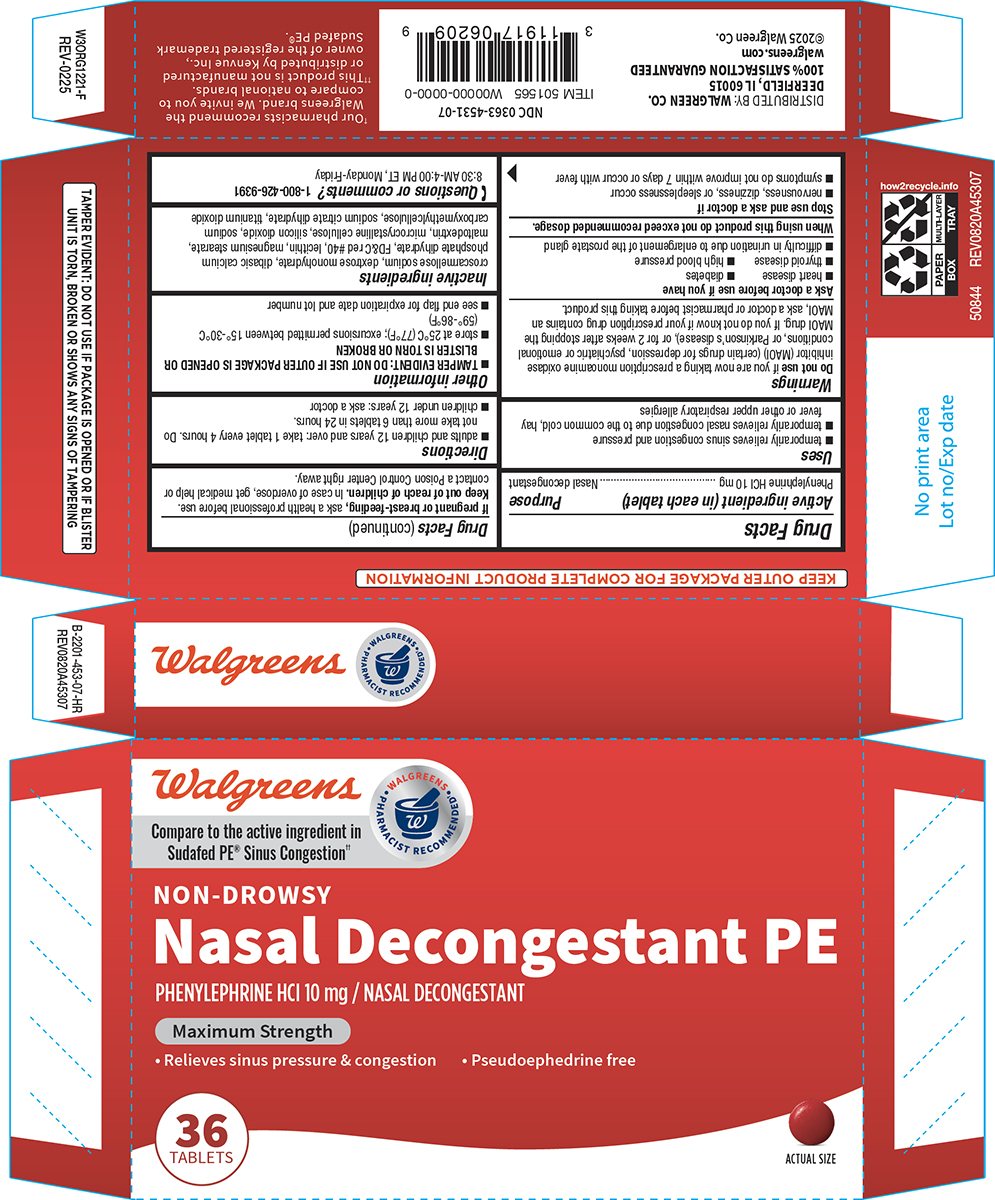 DRUG LABEL: Nasal Decongestant
NDC: 0363-4531 | Form: TABLET, FILM COATED
Manufacturer: Walgreen Company
Category: otc | Type: HUMAN OTC DRUG LABEL
Date: 20250422

ACTIVE INGREDIENTS: PHENYLEPHRINE HYDROCHLORIDE 10 mg/1 1
INACTIVE INGREDIENTS: CROSCARMELLOSE SODIUM; DEXTROSE MONOHYDRATE; DIBASIC CALCIUM PHOSPHATE DIHYDRATE; FD&C RED NO. 40; LECITHIN, SOYBEAN; MAGNESIUM STEARATE; MALTODEXTRIN; MICROCRYSTALLINE CELLULOSE; SILICON DIOXIDE; CARBOXYMETHYLCELLULOSE SODIUM, UNSPECIFIED; TRISODIUM CITRATE DIHYDRATE; TITANIUM DIOXIDE

Walgreens 44-453-Nasal Decongestant

Active ingredient (in each tablet)

Phenylephrine HCl 10 mg

Purpose

Nasal decongestant

Uses

- temporarily relieves sinus congestion and pressure
- temporarily relieves nasal congestion due to the common cold, hay fever or other upper respiratory allergies

Warnings

Do not use

if you are now taking a prescription monoamine oxidase inhibitor (MAOI) (certain drugs for depression, psychiatric or emotional conditions, or Parkinson’s disease), or for 2 weeks after stopping the MAOI drug. If you do not know if your prescription drug contains an MAOI, ask a doctor or pharmacist before taking this product.

Ask a doctor before use if you have

- heart disease
- diabetes
- thyroid disease
- high blood pressure
- difficulty in urination due to enlargement of the prostate gland

When using this product

do not exceed recommended dosage.

Stop use and ask a doctor if

- nervousness, dizziness, or sleeplessness occur
- symptoms do not improve within 7 days or occur with fever

If pregnant or breast-feeding,

ask a health professional before use.

Keep out of reach of children.

In case of overdose, get medical help or contact a Poison Control Center right away.

Directions

- adults and children 12 years and over: take 1 tablet every 4 hours. Do not take more than 6 tablets in 24 hours.
- children under 12 years: ask a doctor

Other information

- TAMPER EVIDENT: DO NOT USE IF OUTER PACKAGE IS OPENED OR BLISTER IS TORN OR BROKEN
- store at 25°C (77°F); excursions permitted between 15°-30°C (59°-86°F)
- see end flap for expiration date and lot number

Inactive ingredients

croscarmellose sodium, dextrose monohydrate, dibasic calcium phosphate dihydrate, FD&C red #40, lecithin, magnesium stearate, maltodextrin, microcrystalline cellulose, silicon dioxide, sodium carboxymethylcellulose, sodium citrate dihydrate, titanium dioxide

Questions or comments?

1-800-426-9391 8:30 AM-4:00 PM ET, Monday-Friday

Principal Display Panel

Walgreens

WALGREENS PHARMACIST RECOMMENDED†

Compare to the active ingredient in
Sudafed PE® Sinus Congestion††

NON-DROWSY
Nasal Decongestant PE
PHENYLEPHRINE HCl 10 mg / NASAL DECONGESTANT

Maximum Strength

• Relieves sinus pressure & congestion • Pseudoephedrine free

36
TABLETS

ACTUAL SIZE

TAMPER EVIDENT: DO NOT USE IF PACKAGE IS OPENED OR IF BLISTER
UNIT IS TORN, BROKEN OR SHOWS ANY SIGNS OF TAMPERING

†Our pharmacists recommend the
Walgreens brand. We invite you to
compare to national brands.
††This product is not manufactured
or distributed by Kenvue Inc.,
owner of the registered trademark
Sudafed PE®.

50844 REV0820A45307

NDC 0363-4531-07

DISTRIBUTED BY: WALGREEN CO.
DEERFIELD, IL 60015
100% SATISFACTION GUARANTEED
walgreens.com
©2025 Walgreen Co.

Walgreens 44-453